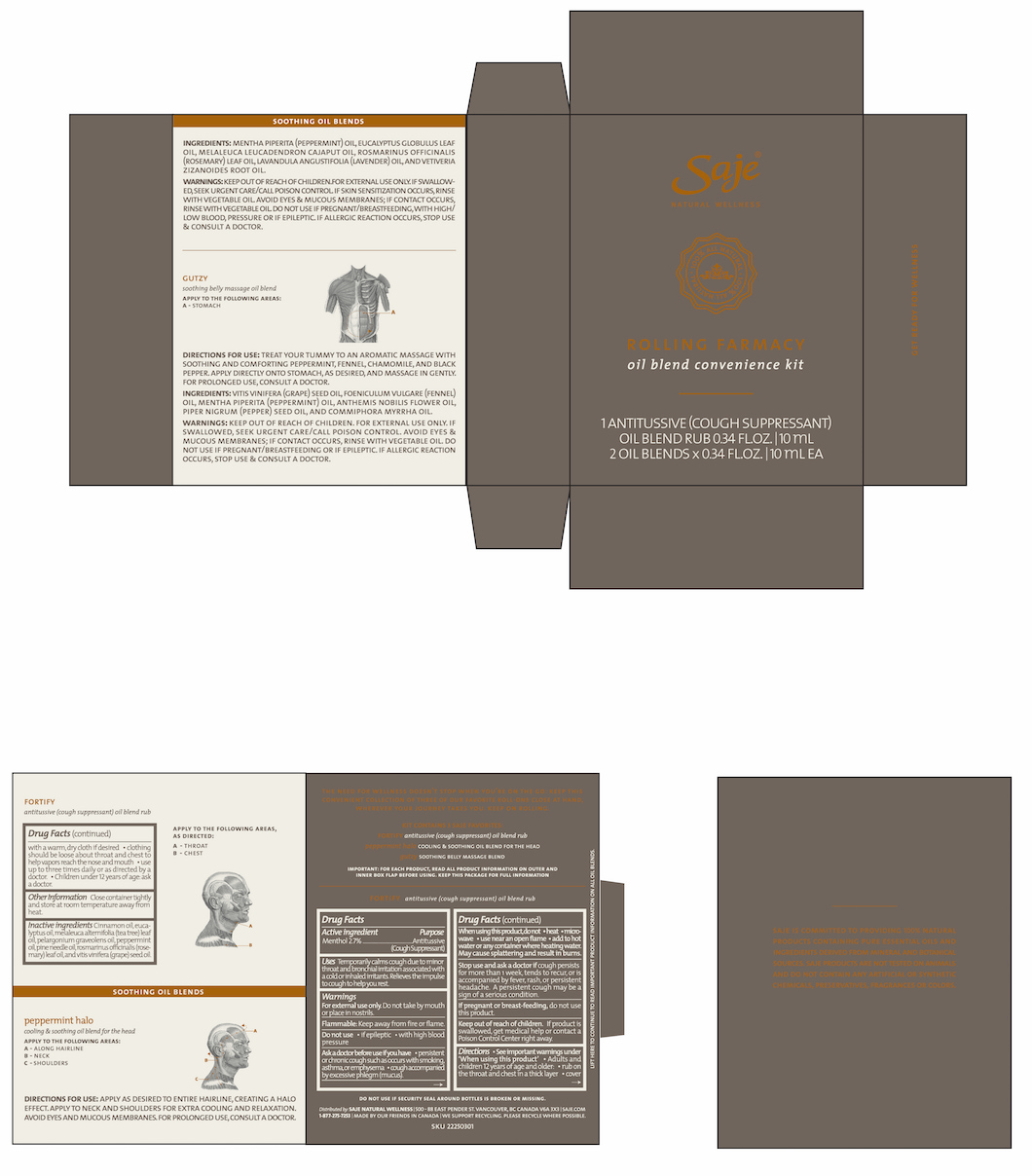 DRUG LABEL: Rolling Farmacy
NDC: 70983-015 | Form: KIT | Route: TOPICAL
Manufacturer: Saje Natural Business Inc.
Category: otc | Type: HUMAN OTC DRUG LABEL
Date: 20260113

ACTIVE INGREDIENTS: MENTHOL 24.03 mg/1 mL
INACTIVE INGREDIENTS: CINNAMON OIL; EUCALYPTUS OIL; TEA TREE OIL; PELARGONIUM GRAVEOLENS FLOWER OIL; PEPPERMINT OIL; PINE NEEDLE OIL (PINUS SYLVESTRIS); ROSEMARY OIL; GRAPE SEED OIL

Rolling Farmacy Oil Blend Convenience Kit (3 x 10 ml)

The need for wellness doesn't stop when you're on the go. Keep this convenient collection of three of our favourit roll-ons close at hand, wherever your journey takes you. Keep on rolling.

Kit Contains 3 Saje Favorites:

FORTIFY antitussive (cough suppressant) oil blend rub

peppermint halo COOLING & SOOTHING OIL BLEND FOR THE HEAD

gutzy SOOTHING BELLY MASSAGE BLEND

IMPORTANT: FOR EACH PRODUCT, READ ALL PRODUCT INFORMATION ON OUTER AND INNER BOX FLAP BEFORE USING. KEEP THIS PACKAGE FOR FULL INFORMATION.

DO NOT USE IF SECURITY SEAL AROUND BOTTLES IS BROKEN OR MISSING

LIFT HERE TO CONTINUE TO READ IMPORTANT PRODUCT INFORMATION ON ALL OIL BLENDS

Distributed by: SAJE NATURAL WELLNESS | 500-88 E. Pender St. Vancouver, BC Canada, V6A 3X3 | saje.com | 1-877-275-7253 | Made by our friends in Canada

We support recycling. Please recycle where possible

GET READY FOR WELLNESS

SKU 22250301

FORTIFY antitussive (cough suppressant) oil blend rub Drug Facts Active ingredient

Menthol 2.7%

Purpose Antitussive (Cough Suppressant)

Uses Temporarily calms cough due to minor throat and bronchial irritation associated with a cold or inhaled irritants. Relieves the impulse to cough to help you rest.

Warnings

For external use only. Do not that by mouth or place in nostrils.

Flammable. Keep away from fire or flame

Do not use

- if epileptic
- with high blood pressure

Ask doctor before use if you have

- persistent or chronic cough such as occurs with smoking, asthma, or emphysema
- cough accompanied by excessive phlegm (mucus).

When using this product, do not

- heat
- microwave
- use near an open flame
- add to hot water or any container where heating water. May cause splattering and result in burns.

Stop use and ask a doctor if

- cough persists for more than 1 week, tends to recur, or is accompanied by fever, rash, or persistent headache. A persistent cough may be a sign of a serious condition.

If pregnant or breast-feeding,

do not use this product.

Keep out of reach of children.

If product is swallowed, get medical help or contact a Poison Control Center right away.

Directions

- See important warnings under 'When using this product'
- Adults and children 12 years or older:
- rub on throat and chest in a thick layer
- cover with warm cloth if desired
- clothing should be loose about throat and chest to help vapors reach the nose and mouth

DOSAGE AND ADMINISTRATION

- use up to three times daily or as directed by a doctor
- Children under 12 years of age: ask a doctor.

Other information

Close container tightly and store at room temperature away from heat .

Inactive ingredients

Cinnamon oil, eucalyptus oil, melaleuca alternifolia (tea tree) leaf oil, pelargonium graveolens oil, peppermint oil, pine needle oil, rosmarinus officinalis (rosemary) leaf oil, and vitis vinifera (grape) seed oil.

FORTIFY antitussive (cough suppressant) oil blend rub

Apply to the following areas, as directed:

A - Throat

B - Chest

SOOTHING OIL BLENDS PEPPERMINT HALO cooling & soothing oil blend for the head

Apply to the following areas:

A - Along hairline

B - Neck

C - Shoulders

Directions for use: Apply as desired to entire hairline, creating a halo effect. Apply to neck and shoulders for extra cooling and relaxation. Avoid eyes and mucous membranes. For prolonged use, consult a doctor.

Ingredients: Mentha piperita (peppermint) oil, eucalyptus globulus leaf oil, melaleuca leucadendron cajaput oil, rosmarinus officinalis (rosemary) leaf oil, lavandula angustifolia (lavender) oil, and vetiveria zizanoides root oil.

Warnings:

- Keep out of reach of children.
- For external use only. if swallowed, seek urgent care/call poison control.
- If skin sensitization occurs, rinse with vegetable oil.
- Avoid eyes & mucous membranes; if contact occurs, rinse with vegetable oil.
- Do not use if pregnant/breastfeeding, with high/low blood pressure, or if epileptic.
- If allergic reaction occurs, stop use & consult a doctor.

GUTZY soothing belly massage blend

Apply to the following areas:

A - Stomach

Directions for use: Treat your tummy to an aromatic massage with soothing and comforting peppermint, fennel, chamomile, and black pepper. apply directly onto stomach, as desired, and massage in gently. For prolonged use, consult a doctor.

Ingredients: vitis vinifera (grape) seed oil, foeniculum vulgare (fennel) oil, mentha piperita (peppermint) oil, anthemis nobilis flower oil, piper nigrum (pepper) seed oil, and commiphora myrrha oil.

Warnings:

- Keep out of reach of children.
- For external use only. if swallowed, seek urgent care/call poison control.
- Avoid eyes & mucous membranes; if contact occurs, rinse with vegetable oil.
- Do not use if pregnant/breastfeeding or if epileptic.
- If allergic reaction occurs, stop use & consult a doctor.

Saje is commited to providing 100% natural products containing pure essentail oils and ingredients derived from mineral and botanical sources. Saje products are not tested on animals and do not contain any artificial or synthetic chemicals, presevatives, fragrances or colors.

PACKAGE LABEL

Saje® Natural Wellness

ROLLING FARMACY

oil blend convenience kit

1 ANTITUSSIVE (COUGH SUPPRESSANT) OIL BLEND RUB 0.34 FL.OZ. | 10 mL

2 OIL BLENDS X 0.34 FL.OZ. | 10 mL EA